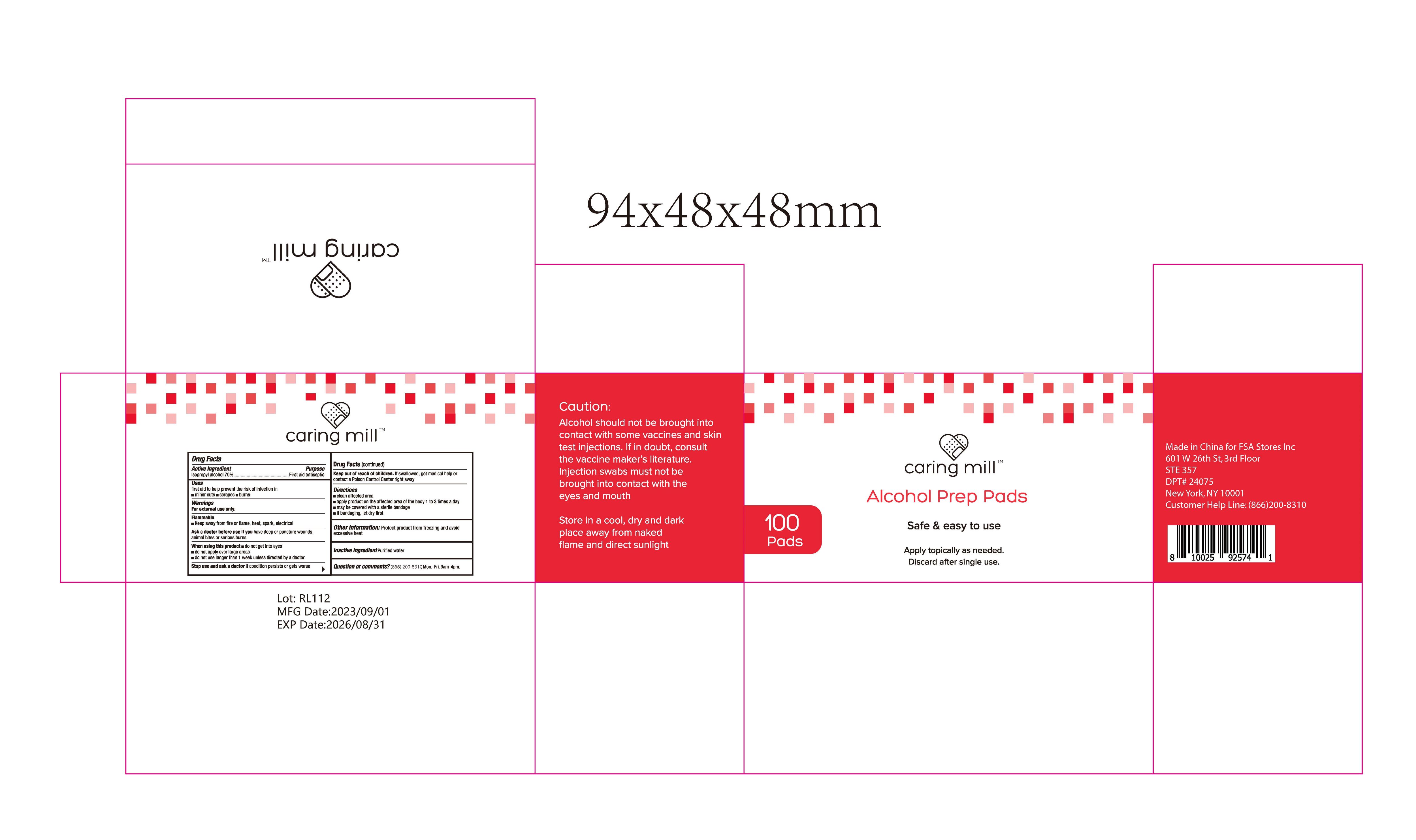 DRUG LABEL: CARING MILL  ALCOHOL PREP PADS
NDC: 78536-010 | Form: CLOTH
Manufacturer: Zhejiang Yiwu Mingou Biotechnology Co., Ltd.
Category: otc | Type: HUMAN OTC DRUG LABEL
Date: 20230829

ACTIVE INGREDIENTS: ISOPROPYL ALCOHOL 70 mL/100 mL
INACTIVE INGREDIENTS: WATER

ACTIVE INGREDIENT

Isopropyl Alcohol 70%

PURPOSE

First aid antiseptic

USE

first aid to help prevent the risk of infection in

minor cuts scrapes burns

Warning

For external use only.
FlammableKeep away from fire or flame, heat, spark, electrical

Ask a doctor before use if you have deep or puncture wounds,animal bites or serious burns
When using this product

do not get into eyesdo not apply over large areas

do not use longer than 1 week unless directed by a doctor
Stop use and ask a doctor if condition persists or gets worse

Keep out of reach of children. lf swallowed, get medical help or
contact a Poison Control Center right away

Directions

clean affected areaapply product on the affected area of the body 1 to 3 times a daymay be covered with a sterile bandageif bandaging, let dry first

Inactive ingredients

Purified water